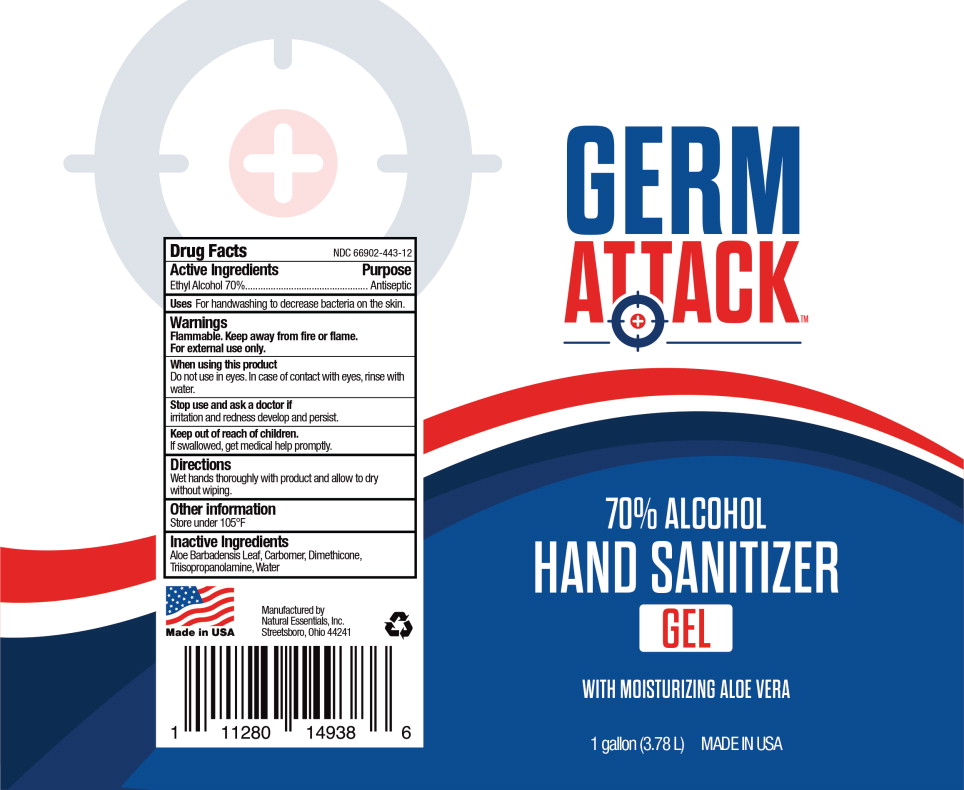 DRUG LABEL: Germ Attack Hand Sanitizer
NDC: 66902-443 | Form: GEL
Manufacturer: Natural Essentials, Inc.
Category: otc | Type: HUMAN OTC DRUG LABEL
Date: 20241004

ACTIVE INGREDIENTS: ALCOHOL 0.7 mL/1 mL
INACTIVE INGREDIENTS: CARBOMER HOMOPOLYMER, UNSPECIFIED TYPE; ALOE VERA LEAF; DIMETHICONE; TRIISOPROPANOLAMINE; WATER

Drug Facts

Active Ingredients

Ethyl Alcohol 70%

Purpose

Antiseptic

Uses

For handwashing to decrease bacteria on the skin.

Warnings

Flammable. Keep away from fire or flame.

For external use only.

When using this product

Do not use in eyes. In case of contact with eyes, rinse with water.

Stop use and ask a doctor if

irritation and redness develop and persist.

Keep out of reach of children.

If swallowed, get medical help promptly.

Directions

Wet hands thoroughly with product and allow to dry without wiping.

Other information

Store under 105°F

Inactive Ingredients

Aloe Barbadensis Leaf, Carbomer, Dimethicone, Triisopropanolamine, Water

Principal Display Panel – Jug Label

GERM
ATTACK ™

70% ALCOHOL

HAND SANITIZER

GEL

WITH MOISTURIZING ALOE VERA

1 gallon (3.78 L) MADE IN USA